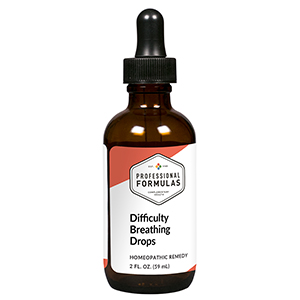 DRUG LABEL: Difficulty Breathing Drops
NDC: 63083-2171 | Form: LIQUID
Manufacturer: Professional Complementary Health Formulas
Category: homeopathic | Type: HUMAN OTC DRUG LABEL
Date: 20190815

ACTIVE INGREDIENTS: BEEF LUNG 6 [hp_X]/59 mL; PLANTAGO MAJOR WHOLE 6 [hp_X]/59 mL; BOS TAURUS INTERVERTEBRAL DISC 6 [hp_X]/59 mL; SILICON DIOXIDE 8 [hp_X]/59 mL; CONIUM MACULATUM FLOWERING TOP 9 [hp_X]/59 mL; ANTIMONY POTASSIUM TARTRATE 12 [hp_X]/59 mL; SILVER NITRATE 12 [hp_X]/59 mL; SELENICEREUS GRANDIFLORUS STEM 12 [hp_X]/59 mL; BLACK COHOSH 12 [hp_X]/59 mL; BEEF SHORT PLATE 12 [hp_X]/59 mL; MOSCHUS MOSCHIFERUS MUSK SAC RESIN 12 [hp_X]/59 mL; AMARYLLIS BELLADONNA WHOLE 30 [hp_X]/59 mL; COPPER 30 [hp_X]/59 mL; DAPHNE MEZEREUM BARK 30 [hp_X]/59 mL; TOXICODENDRON PUBESCENS LEAF 30 [hp_X]/59 mL; HYOSCYAMUS NIGER 200 [hp_X]/59 mL; DATURA STRAMONIUM 200 [hp_X]/59 mL
INACTIVE INGREDIENTS: ALCOHOL; WATER

C171

ACTIVE INGREDIENTS

Lung 6X
Plantago major 6X
Thoracic vertebrae 6X
Silicea 8X
Conium maculatum 9X
Antimonium tartaricum 12X
Argentum nitricum 12X
Cactus grandiflorus 12X
Cimicifuga racemosa 12X
Diaphragm 12X
Moschus 12X
Belladonna 30X
Cuprum metallicum 30X
Mezereum 30X
Rhus toxicodendron 30X
Hyoscyamus niger 200X
Stramonium 200X

QUESTIONS

Professional Formulas

PO Box 2034 Lake Oswego, OR 97035

INDICATIONS

For the temporary relief of nasal or chest congestion, runny nose, itchy or watery eyes, cough, wheezing, or shortness of breath.*

PURPOSE

*Claims based on traditional homeopathic practice, not accepted medical evidence. Not FDA evaluated.

WARNINGS

Consult a doctor if condition worsens or if symptoms persist. Keep out of the reach of children. In case of overdose, get medical help or contact a poison control center right away. If pregnant or breastfeeding, ask a healthcare professional before use.

Keep out of the reach of children.

PREGNANCY OR BREAST FEEDING

If pregnant or breastfeeding, ask a healthcare professional before use.

DIRECTIONS

Place drops under tongue 30 minutes before/after meals. Adults and children 12 years and over: Take 10 drops up to 3 times per day for up to 6 weeks. For immediate onset of symptoms, take 10 to 15 drops every 15 minutes up to 3 hours. For less severe symptoms, take 10-15 drops hourly up to 8 hours. Consult a physician for use in children under 12 years of age.

OTHER INFORMATION

Tamper resistant. If seal is broken, do not use. After opening, close container tightly and store at room temperature away from heat.

INACTIVE INGREDIENTS

20% ethanol, purified water.

LABEL

Est 1985

Professional Formulas

Complementary Health

Difficulty Breathing Drops

Homeopathic Remedy

2 FL. OZ. (59 mL)